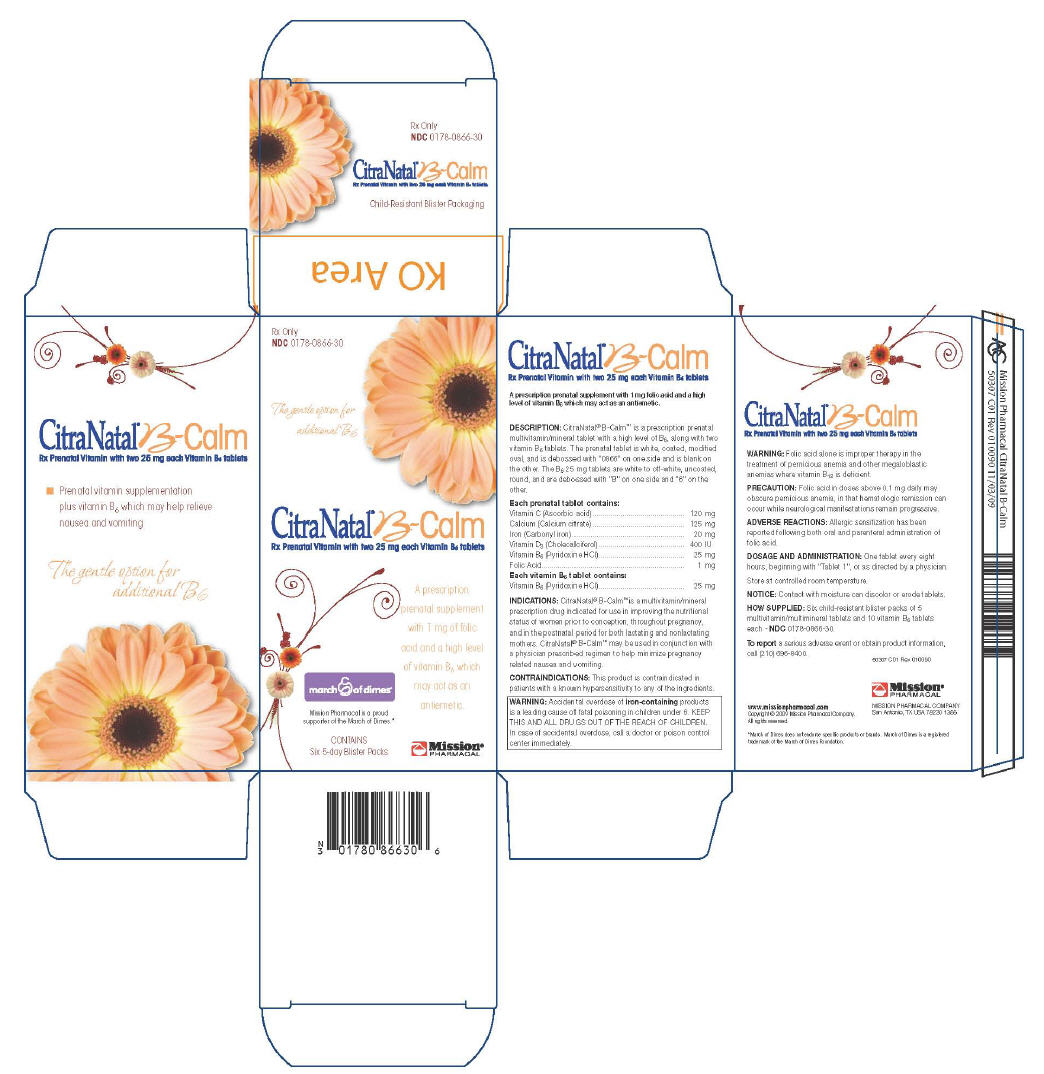 DRUG LABEL: CitraNatal
NDC: 0178-0866 | Form: KIT | Route: ORAL
Manufacturer: Mission Pharmacal Company
Category: prescription | Type: HUMAN PRESCRIPTION DRUG LABEL
Date: 20100503

ACTIVE INGREDIENTS: ascorbic acid 120 mg/1 1; calcium citrate 125 mg/1 1; Iron Pentacarbonyl 20 mg/1 1; Cholecalciferol 400 [iU]/1 1; Pyridoxine Hydrochloride 25 mg/1 1; folic acid 1 mg/1 1; Pyridoxine Hydrochloride 25 mg/1 1
INACTIVE INGREDIENTS: Polyethylene Glycol; Cellulose, Microcrystalline; Povidone; Hypromelloses; Titanium Dioxide; Magnesium Silicate; Magnesium Stearate; Vitamin A Palmitate; Cellulose, Microcrystalline; Povidone; Magnesium Stearate

CitraNatal®B-Calm
Rx Prenatal Vitamin with two 25 mg each Vitamin B6 tablets

A prescription prenatal supplement with 1 mg folic acid and a high level of vitamin B6 which may act as an antiemetic.

DESCRIPTION

CitraNatal® B-Calm™ is a prescription prenatal multivitamin/mineral tablet with a high level of B6, along with two vitamin B6 tablets. The prenatal tablet is white, coated, modified oval, and is debossed with "0866" on one side and is blank on the other. The B6 25 mg tablets are white to off-white, uncoated, round, and are debossed with "B" on one side and "6" on the other.

Each prenatal tablet contains:

Vitamin C (Ascorbic acid) | 120 mg
Calcium (Calcium citrate) | 125 mg
Iron (Carbonyl iron) | 20 mg
Vitamin D3 (Cholecalciferol) | 400 IU
Vitamin B6 (Pyridoxine HCl) | 25 mg
Folic Acid | 1 mg

Each vitamin B6 tablet contains:

Vitamin B6 (Pyridoxine HCl) | 25 mg

INDICATIONS

CitraNatal® B-Calm™ is a multivitamin/mineral prescription drug indicated for use in improving the nutritional status of women prior to conception, throughout pregnancy, and in the postnatal period for both lactating and nonlactating mothers. CitraNatal® B-Calm™ may be used in conjunction with a physician prescribed regimen to help minimize pregnancy related nausea and vomiting.

CONTRAINDICATIONS

This product is contraindicated in patients with a known hypersensitivity to any of the ingredients.

WARNING

Accidental overdose of iron-containing products is a leading cause of fatal poisoning in children under 6. KEEP THIS AND ALL DRUGS OUT OF THE REACH OF CHILDREN. In case of accidental overdose, call a doctor or poison control center immediately.

WARNING

Folic acid alone is improper therapy in the treatment of pernicious anemia and other megaloblastic anemias where vitamin B12 is deficient.

PRECAUTION

Folic acid in doses above 0.1 mg daily may obscure pernicious anemia, in that hematologic remission can occur while neurological manifestations remain progressive.

ADVERSE REACTIONS

Allergic sensitization has been reported following both oral and parenteral administration of folic acid.

DOSAGE AND ADMINISTRATION

One tablet every eight hours, beginning with "Tablet 1", or as directed by a physician.

Store at controlled room temperature.

NOTICE: Contact with moisture can discolor or erode tablets.

HOW SUPPLIED

Six child-resistant blister packs of 5 multivitamin/multimineral tablets and 10 vitamin B6 tablets each - NDC 0178-0866-30.

To report a serious adverse event or obtain product information, call (210) 696-8400.

50307 C01 REV 010090

MISSION PHARMACAL COMPANY
San Antonio, TX USA 78230 1355

www.missionpharmacal.com
Copyright © 2009 Mission Pharmacal Company.
All rights reserved.

*March of Dimes does not endorse specific products or brands. March of dimes is a registered trademark of the March of Dimes Foundation.

PRINCIPAL DISPLAY PANEL

Rx Only
NDC 0178-0866-30

The gentle option for
additional B6

CitraNatal® B-Calm
Rx Prenatal Vitamin with two 25 mg each Vitamin B6 tablets

A prescription
prenatal supplement
with 1 mg of folic
acid and a high level
of vitamin B6 which
may act as an
antiemetic.

march of dimes®

Mission Pharmacal is a proud
supporter of the March of Dimes.®

CONTAINS
Six 5-day Blister Packs

Mission®
PHARMACAL